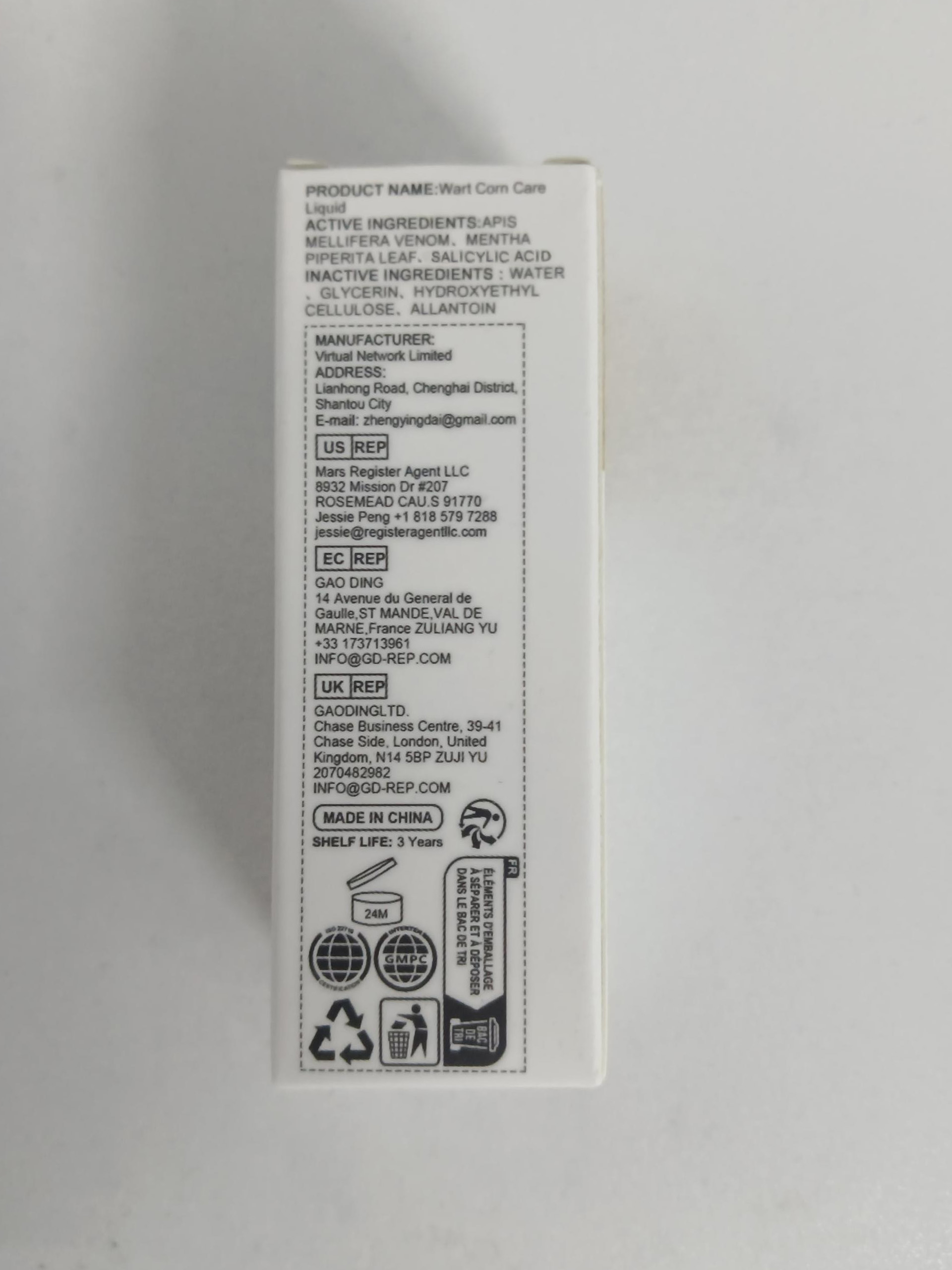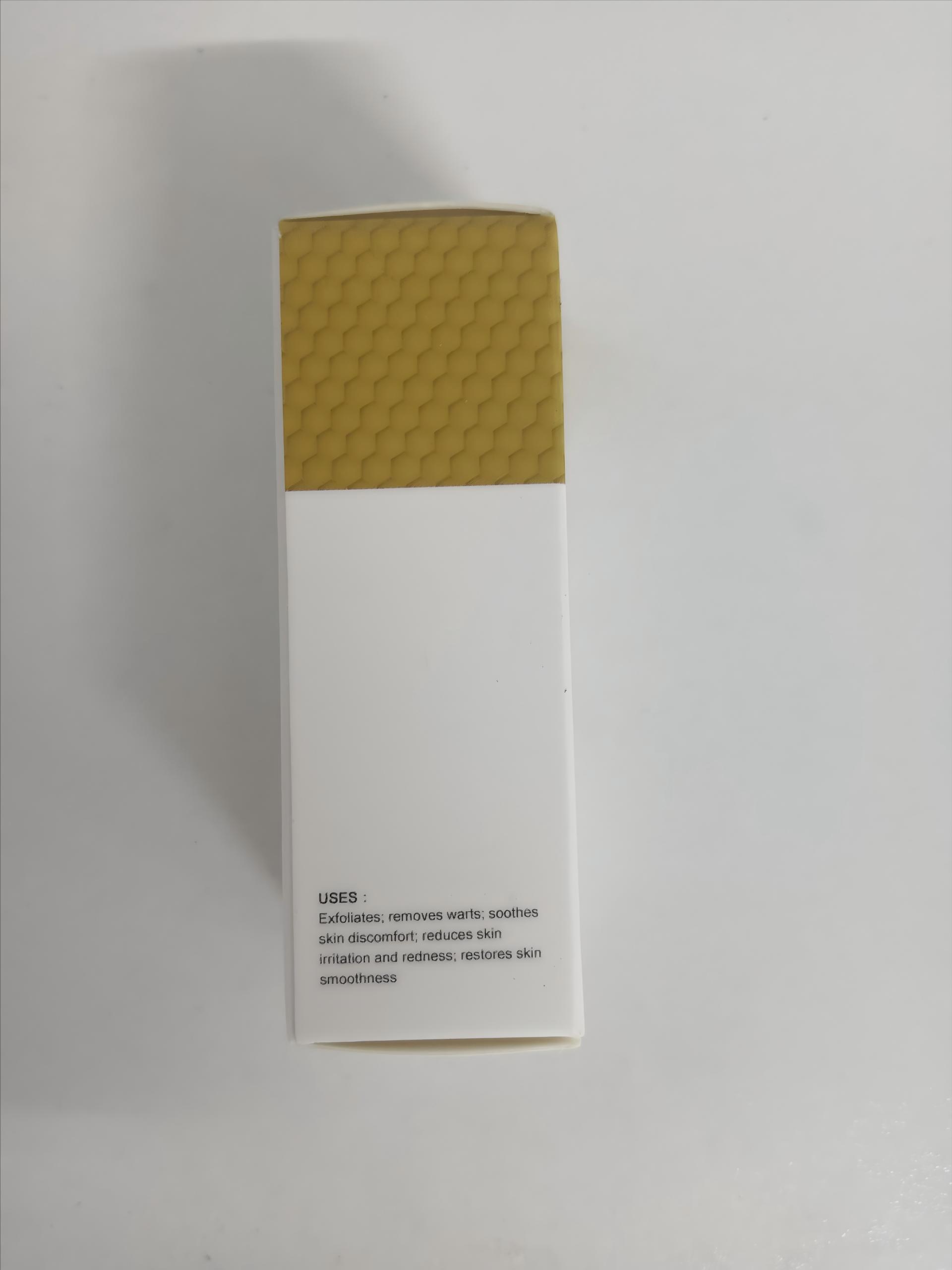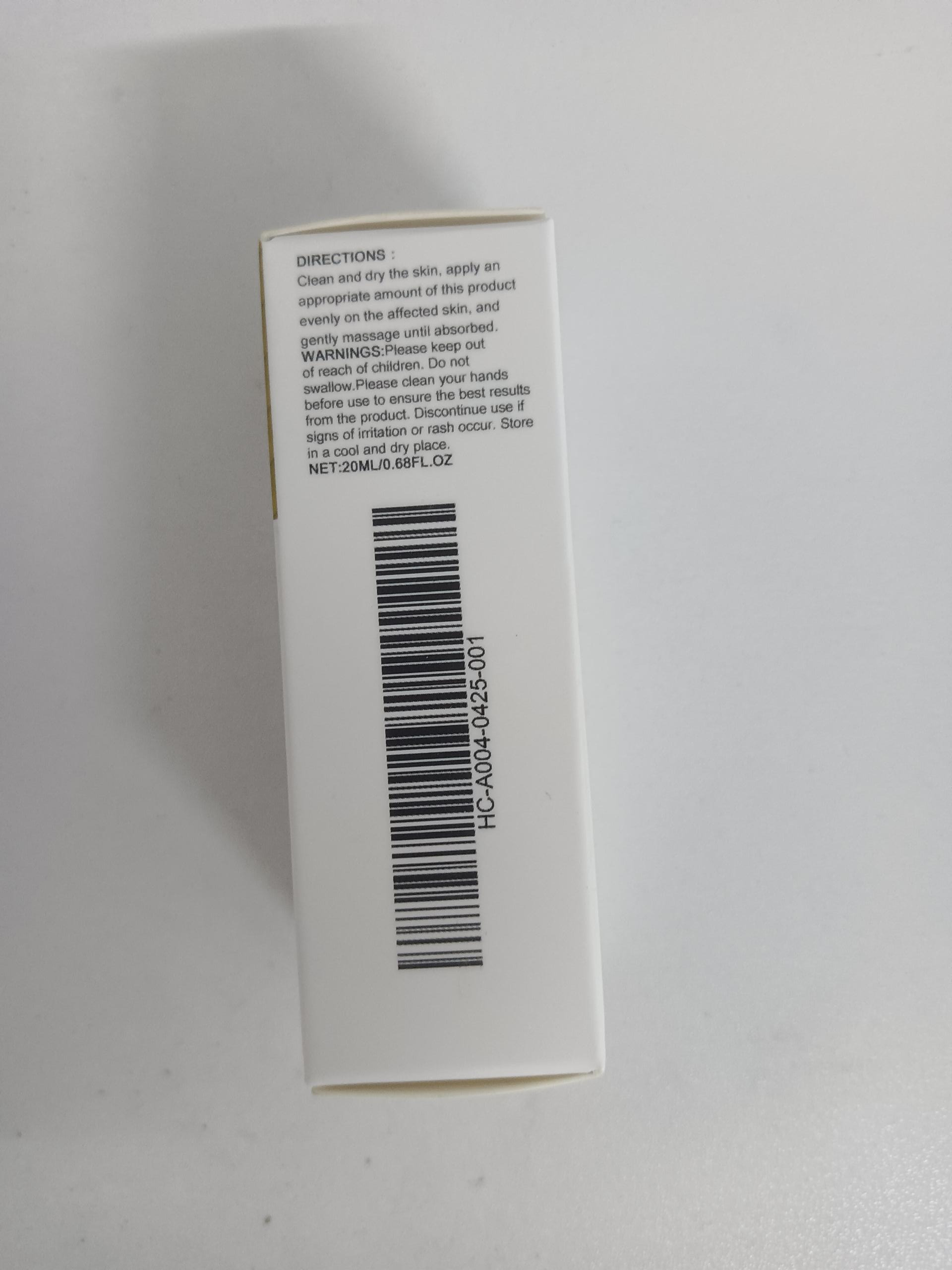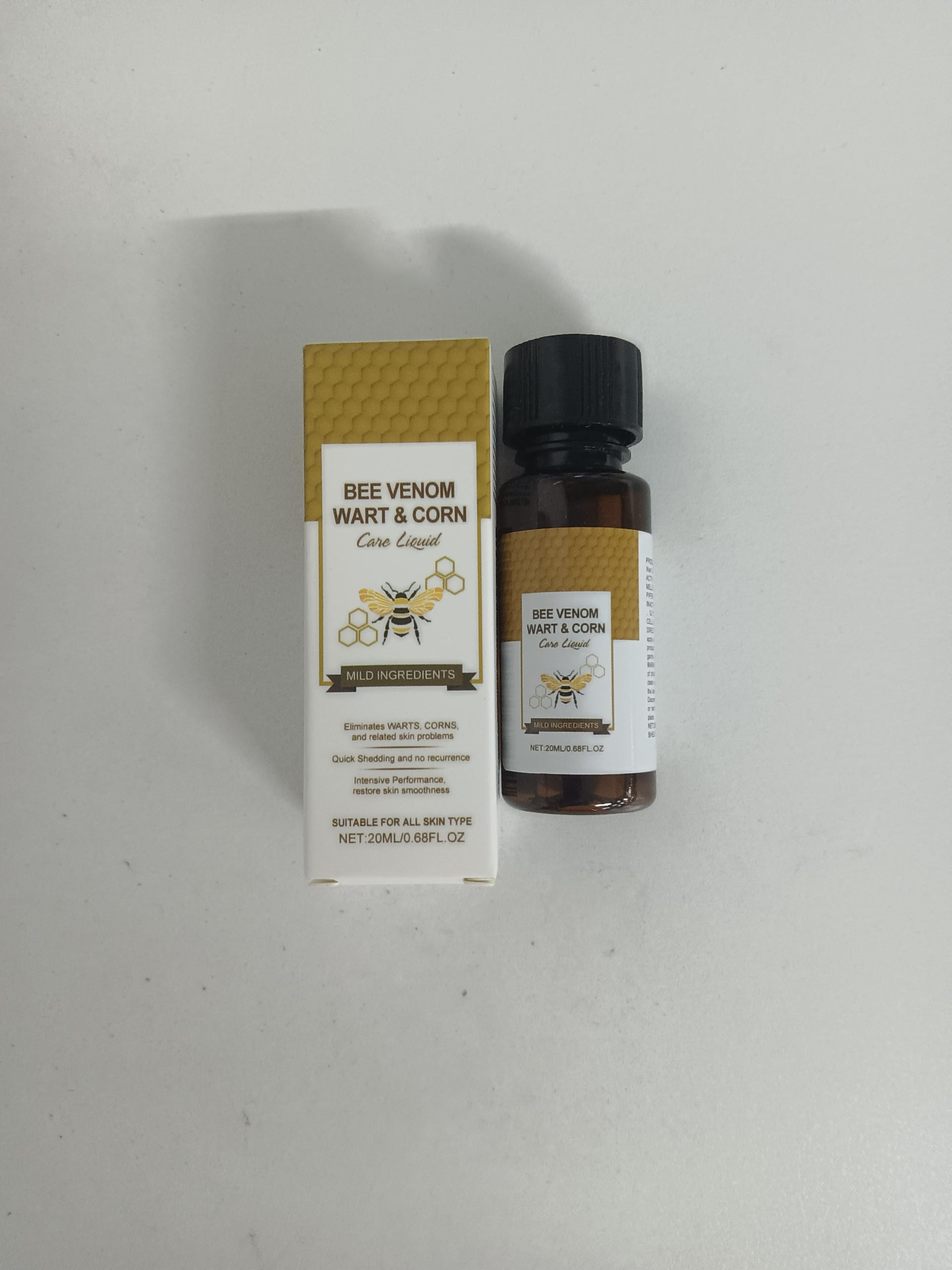 DRUG LABEL: dasWagen Wart Remover Liquid
NDC: 84660-115 | Form: LIQUID
Manufacturer: Guangdong Ximonth Technology Co., Ltd.
Category: otc | Type: HUMAN OTC DRUG LABEL
Date: 20250930

ACTIVE INGREDIENTS: SALICYLIC ACID 17 g/100 mL
INACTIVE INGREDIENTS: WATER; GLYCERIN; (2-HYDROXYETHYL)(HYDROXYMETHYL)AMINE; CELLULOSE, OXIDIZED

dasWagen Wart Remover Liquid